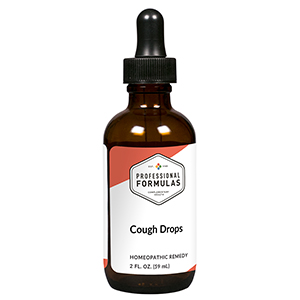 DRUG LABEL: Cough Drops
NDC: 63083-2014 | Form: LIQUID
Manufacturer: Professional Complementary Health Formulas
Category: homeopathic | Type: HUMAN OTC DRUG LABEL
Date: 20190815

ACTIVE INGREDIENTS: SPONGIA OFFICINALIS SKELETON, ROASTED 2 [hp_X]/59 mL; AMARYLLIS BELLADONNA WHOLE 3 [hp_X]/59 mL; IPECAC 3 [hp_X]/59 mL; RUMEX CRISPUS ROOT 3 [hp_X]/59 mL; POLYGALA SENEGA WHOLE 3 [hp_X]/59 mL; POTASSIUM SULFATE 4 [hp_X]/59 mL; MENTHA X PIPERITA WHOLE 4 [hp_X]/59 mL; PULSATILLA MONTANA WHOLE 4 [hp_X]/59 mL; ARSENIC TRIIODIDE 6 [hp_X]/59 mL; DROSERA ROTUNDIFOLIA WHOLE 6 [hp_X]/59 mL; CALCIUM SULFIDE 6 [hp_X]/59 mL; SANGUINARIA CANADENSIS ROOT 6 [hp_X]/59 mL; BRYONIA ALBA ROOT 12 [hp_X]/59 mL; POTASSIUM DICHROMATE 12 [hp_X]/59 mL
INACTIVE INGREDIENTS: ALCOHOL; WATER

C14

ACTIVE INGREDIENTS

Spongia tosta 2X
Belladonna 3X
Ipecacuanha 3X
Rumex crispus 3X
Senega officinalis 3X
Kali sulphuricum 4X
Mentha piperita 4X
Pulsatilla 4X
Arsenicum iodatum 6X
Drosera rotundifolia 6X
Hepar sulphuris calcareum 6X
Sanguinaria canadensis 6X
Bryonia 12X
Kali bichromicum 12X

QUESTIONS

Professional Formulas

PO Box 2034 Lake Oswego, OR 97035

INDICATIONS

Temporarily reduces the intensity of coughing.*

PURPOSE

*Claims based on traditional homeopathic practice, not accepted medical evidence. Not FDA evaluated.

WARNINGS

A persistent cough may be a sign of a serious condition. If cough persists, tends to recur, or is accompanied by a fever, rash, or other symptoms, consult a doctor. Keep out of the reach of children. In case of overdose, get medical help or contact a poison control center right away. If pregnant or breastfeeding, ask a healthcare professional before use.

Keep out of the reach of children.

PREGNANCY OR BREAST FEEDING

If pregnant or breastfeeding, ask a healthcare professional before use.

DIRECTIONS

Place drops under tongue 30 minutes before/after meals. Adults and children 12 years and over: Take 10 drops up to 3 times per day for up to 6 weeks. For immediate onset of symptoms, take 10 to 15 drops every 15 minutes up to 3 hours. For less severe symptoms, take 10-15 drops hourly up to 8 hours. Consult a physician for use in children under 12 years of age.

OTHER INFORMATION

Tamper resistant. If seal is broken, do not use. After opening, close container tightly and store at room temperature away from heat.

INACTIVE INGREDIENTS

20% ethanol, purified water.

LABEL

Est 1985

Professional Formulas

Complementary Health

Cough Drops

Homeopathic Remedy

2 FL. OZ. (59 mL)